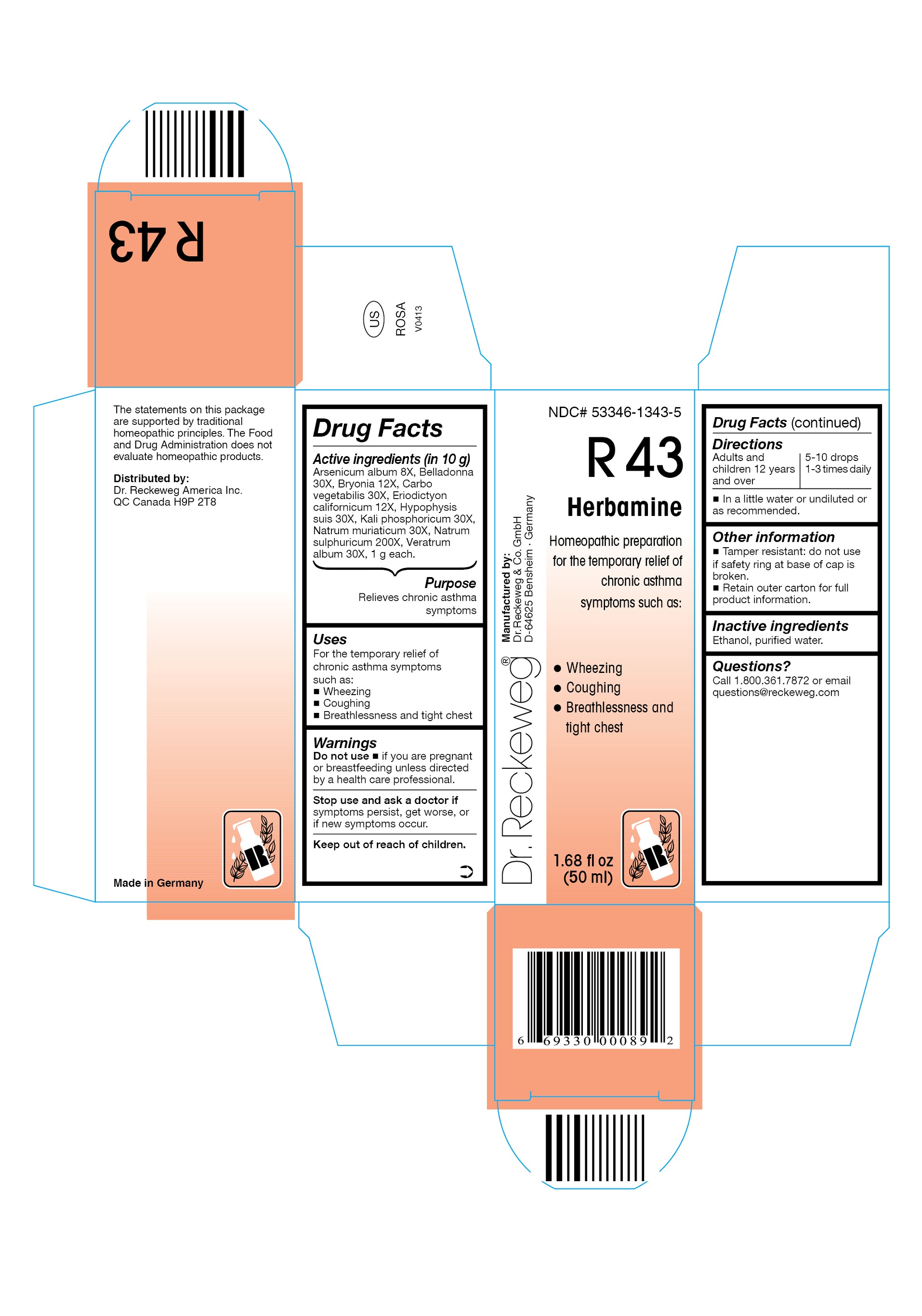 DRUG LABEL: DR. RECKEWEG R43 Herbamine
NDC: 53346-1343 | Form: LIQUID
Manufacturer: PHARMAZEUTISCHE FABRIK DR. RECKEWEG & CO
Category: homeopathic | Type: HUMAN OTC DRUG LABEL
Date: 20130405

ACTIVE INGREDIENTS: ARSENIC TRIOXIDE 8 [hp_X]/50 mL; ATROPA BELLADONNA 30 [hp_X]/50 mL; BRYONIA DIOICA ROOT 12 [hp_X]/50 mL; ACTIVATED CHARCOAL 30 [hp_X]/50 mL; ERIODICTYON CALIFORNICUM FLOWERING TOP 12 [hp_X]/50 mL; SUS SCROFA PITUITARY GLAND 30 [hp_X]/50 mL; POTASSIUM PHOSPHATE, DIBASIC 30 [hp_X]/50 mL; SODIUM CHLORIDE 30 [hp_X]/50 mL; SODIUM SULFATE 200 [hp_X]/50 mL; VERATRUM ALBUM ROOT 30 [hp_X]/50 mL
INACTIVE INGREDIENTS: ALCOHOL; WATER

DR. RECKEWEG R43 Herbamine

Active ingredients

Arsenicum album 8X, Belladonna 30X, Bryonia 12X, Carbo vegetabilis 30X, Eriodictyon californicum 12X, Hypophysis suis 30X, Kali phosphoricum 30X, Natrum muriaticum 30X, Natrum sulphuricum 200X, Veratrum album 30X, 1 g each in 10 g.

Purpose

Relieves chronic asthma symptoms

Uses

For the temporary relief of chronic asthma symptoms such as:

- Wheezing
- Coughing
- Breathlessness and tight chest

Warnings

Do not use

- if you are pregnant or breastfeeding unless directed by a health care professional.

Stop use and ask a doctor if symptoms persist, get worse, or if new symptoms occur.

Keep out of reach of children.

Directions

Adults and children ≥ 12 years 5-10 drops 1-3 times daily in a little water or undiluted or as recommended.

Other information

- Tamper resistant: do not use if safety ring at base of cap is broken.
- Retain outer carton for full product information.

Inactive ingredients

Ethanol, purified water.

Questions?

Call 1-800-361-7872 or email questions@reckeweg.com

PACKAGE LABEL

NDC# 53346-1343-5

Dr. Reckeweg R43 Herbamine

Homeopathic preparation for the temporary relief of chronic asthma symptoms such as:

- Wheezing
- Coughing
- Breathlessness and tight chest

Manufactured by:

Dr. Reckeweg Co. GmbH

D-64625 Bensheim

Germany

1.68 fl oz
(50 ml)